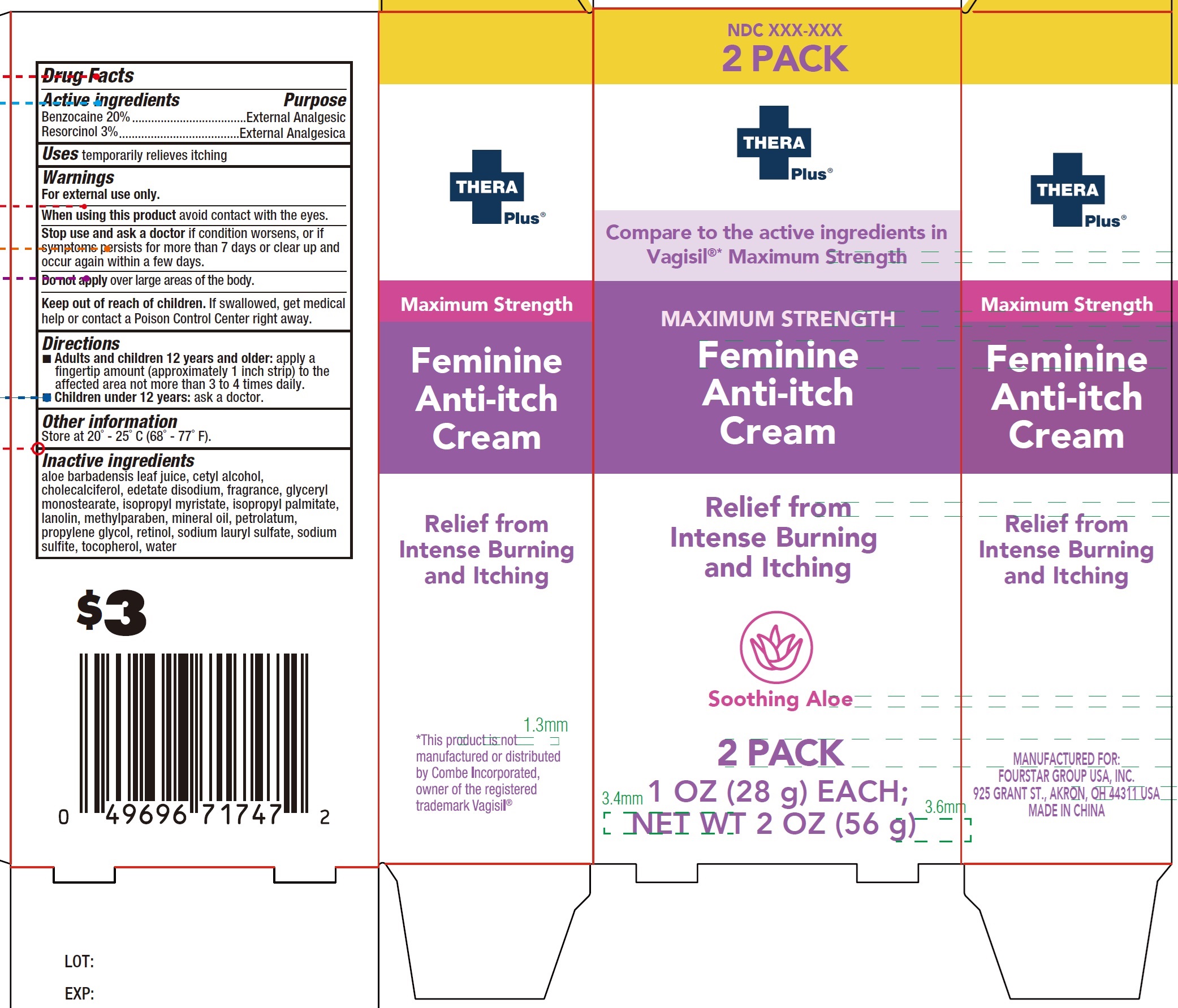 DRUG LABEL: Thera Plus Maximum Strength Feminine Anti-Itch
NDC: 80684-142 | Form: CREAM
Manufacturer: FOURSTAR GROUP USA, INC.
Category: otc | Type: HUMAN OTC DRUG LABEL
Date: 20250226

ACTIVE INGREDIENTS: BENZOCAINE 200 mg/1 g; RESORCINOL 30 mg/1 g
INACTIVE INGREDIENTS: ALOE VERA LEAF; CETYL ALCOHOL; CHOLECALCIFEROL; EDETATE DISODIUM; GLYCERYL MONOSTEARATE; ISOPROPYL MYRISTATE; ISOPROPYL PALMITATE; LANOLIN; METHYLPARABEN; MINERAL OIL; PETROLATUM; PROPYLENE GLYCOL; RETINOL; SODIUM LAURYL SULFATE; SODIUM SULFITE; TOCOPHEROL; WATER

Thera Plus Maximum Strength Feminine Anti-Itch Cream

Active ingredients

Benzocaine 20%
Resorcinol 3%

Purpose

External Analgesic

Uses

temporarily relieves itching

Warnings

For external use only.

When using this product

avoid contact with the eyes.

Stop use and ask a doctor

if condition worsens, or if symptoms persists for more than 7 days or clear up and occur again within a few days.

Do not applyover large areas of the body.

Keep out of reach of children.

If swallowed, get medical help or contact a Poison Control Center right away.

Directions

- Adults and children 12 years and older:apply a fingertip amount (approximately 1 inch strip) to the affected area not more than 3 to 4 times daily.

- Children under 12 years:ask a doctor.

Other information

Store at 20° - 25° C (68° - 77° F).

Inactive ingredientsa

aloe barbadensis leaf juice, cetyl alcohol, cholecalciferol, edetate disodium, fragrance, glyceryl monostearate, isopropyl myristate, isopropyl palmitate, lanolin, methylparaben, mineral oil, petrolatum, propylene glycol, retinol, sodium lauryl sulfate, sodium sulfite, tocopherol, water